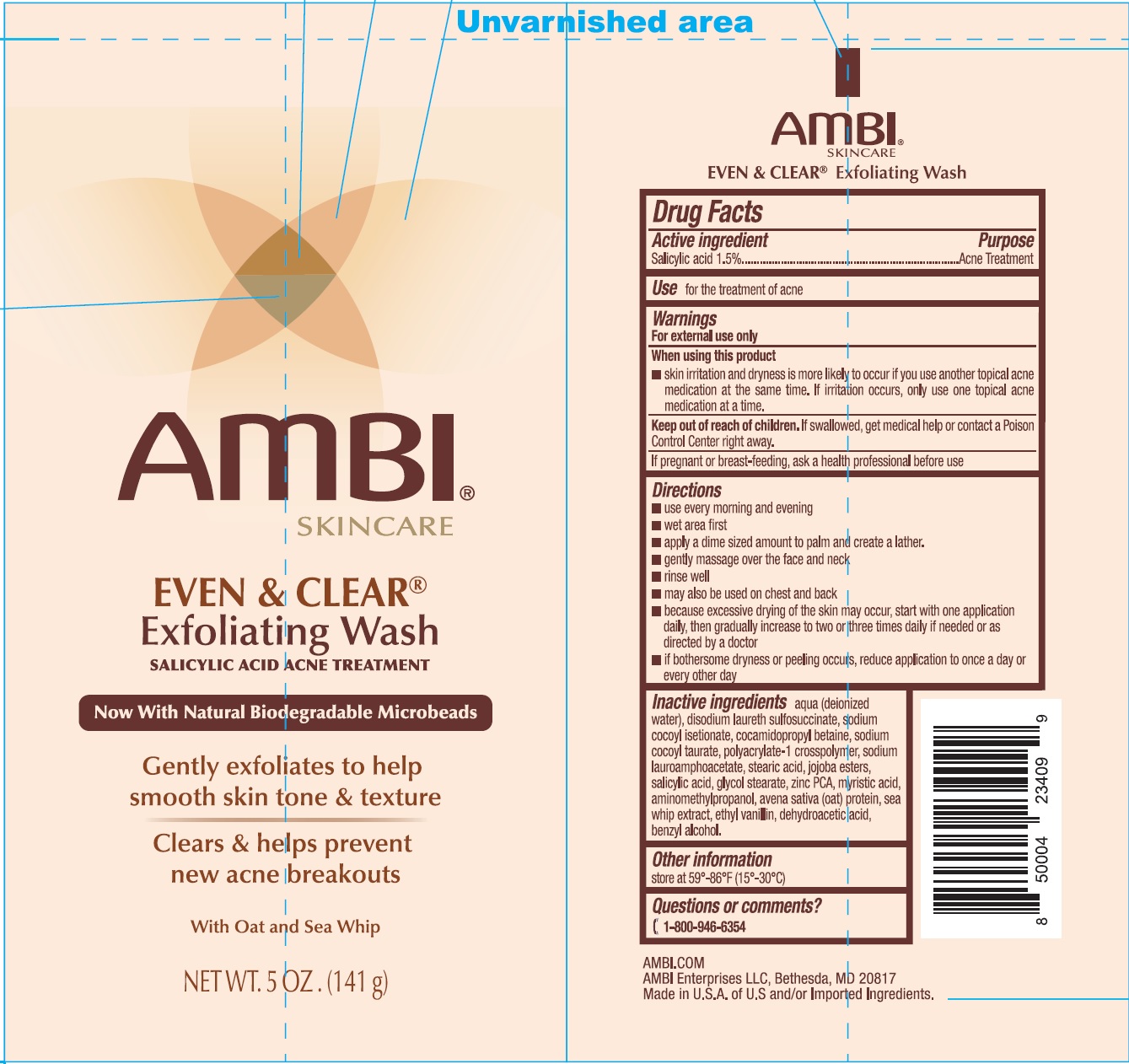 DRUG LABEL: AMBI Even and Clear Exfoliating Wash Acne Treatment
NDC: 73453-166 | Form: GEL
Manufacturer: AMBI ENTERPRISES, LLC
Category: otc | Type: HUMAN OTC DRUG LABEL
Date: 20250724

ACTIVE INGREDIENTS: SALICYLIC ACID 15 mg/1 g
INACTIVE INGREDIENTS: WATER; DISODIUM LAURETH SULFOSUCCINATE; SODIUM COCOYL ISETHIONATE; COCAMIDOPROPYL BETAINE; SODIUM LAUROAMPHOACETATE; STEARIC ACID; GLYCOL STEARATE; ZINC PIDOLATE; MYRISTIC ACID; OAT; PSEUDOPTEROGORGIA ELISABETHAE; ETHYL VANILLIN; DEHYDROACETIC ACID; BENZYL ALCOHOL

AMBI Even & Clear Exfoliating Wash Acne Treatment

Active ingredient

Salicylic acid 1.5%

Purpose

Acne Treatment

Use

for the treatment of acne

Warnings

For external use only

When using this product

skin irritation and dryness is more likely to occur if you use another topical acne medication at the same time. If irritation occurs, only use one topical acne medication at a time.

Keep out of reach of children.

If swallowed, get medical help or contact a Poison Control Center right away.

If pregnant or breast-feeding,

ask a health professional before use

Directions

- use every morning and evening
- wet area first
- apply a dime sized amount to palm and create a lather.
- gently massage over the face and neck
- rinse well
- may also be used on chest and back
- because excessive drying of the skin may occur, start with one application daily, then gradually increase to two or three times daily if needed or as directed by a doctor
- if bothersome dryness or peeling occurs, reduce application to once a day or every other day

Inactive ingredients

aqua (deionized water), disodium laureth sulfosuccinate, sodium cocoyl isetionate, cocamidopropyl betaine, sodium cocoyl taurate, polyacrylate-1 crosspolymer, sodium lauroamphoacetate, stearic acid, jojoba esters, salicylic acid, glycol stearate, zinc PCA, myristic acid, aminomethyl propanol avena sativa (oat) protein, sea whip extract, ethyl vanillin, dehydroacetic acid, benzyl alcohol.

Other information

store at 59°-86°F (15°-30°C)

Questions or comments

1-800-946-6354